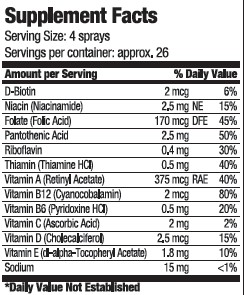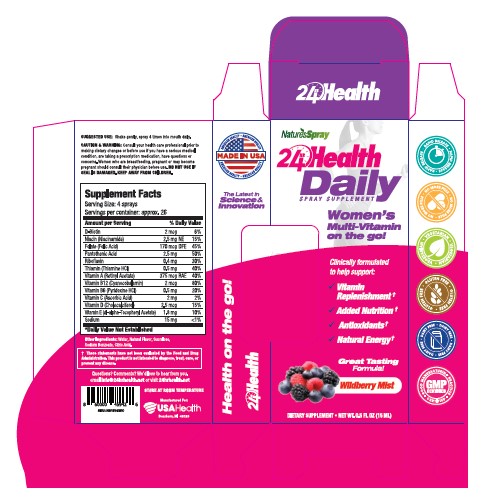 DRUG LABEL: 24hr Health Daily Women
NDC: 80893-002 | Form: SPRAY
Manufacturer: USA Health
Category: other | Type: Dietary Supplement
Date: 20201029

ACTIVE INGREDIENTS: BIOTIN 2 ug/15 mL; NIACINAMIDE 2.5 mg/15 mL; FOLIC ACID 170 ug/15 mL; PANTOTHENIC ACID 2.5 mg/15 mL; RIBOFLAVIN .4 mg/15 mL; THIAMINE .5 mg/15 mL; VITAMIN A 375 ug/15 mL; CYANOCOBALAMIN 2 ug/15 mL; PYRIDOXINE HYDROCHLORIDE .5 mg/15 mL; ASCORBIC ACID 2 mg/15 mL; CHOLECALCIFEROL 2.5 ug/15 mL; .ALPHA.-TOCOPHEROL ACETATE, D- 1.8 mg/15 mL; SODIUM 15 mg/15 mL
INACTIVE INGREDIENTS: water; SUCRALOSE; SODIUM BENZOATE; CITRIC ACID MONOHYDRATE

24hr Health Daily Women

Purpose

Clinically formulated to help support

- Vitamin Replenishment
- Added Nutrition
- Antioxidants
- Natural Energy

Precaution

Consult your health care professional prior to making dietary changes or before use if you have a serious medical condition, are taking a prescription medicine, have questions or concerns.

Warning

Women who are breastfeeding, pregnant, or may become pregnant should consult their physician before use.

Safe Handling

Do not use if damaged. Keep away from children.

Dosage

Shake gently. Spray 4 times into mouth daily.